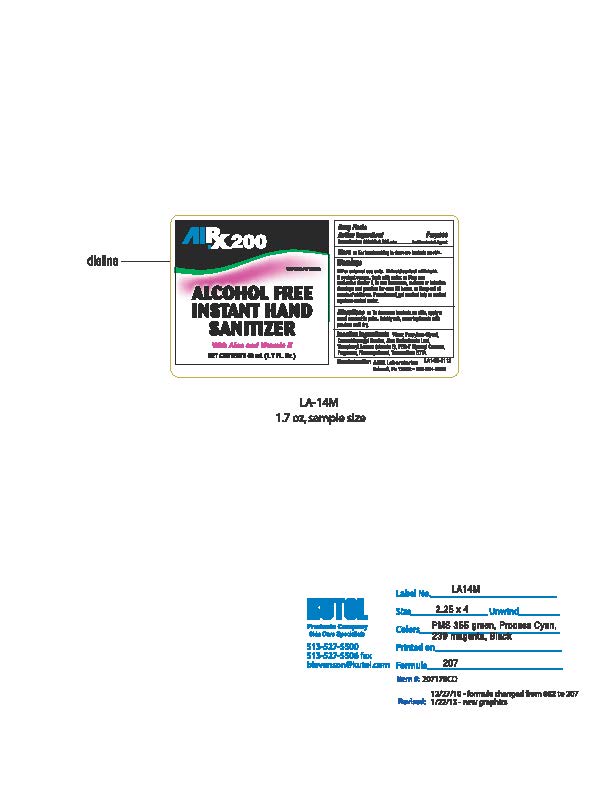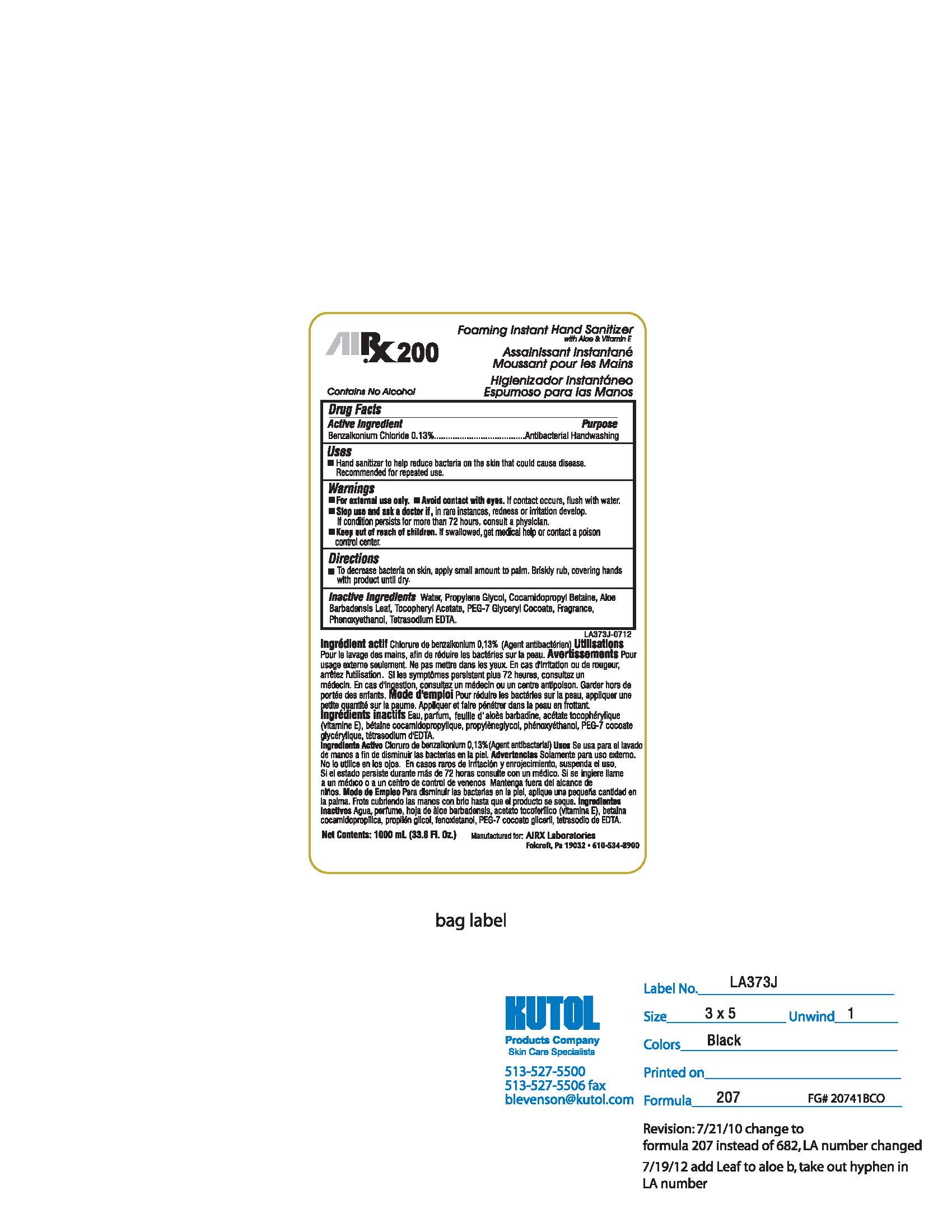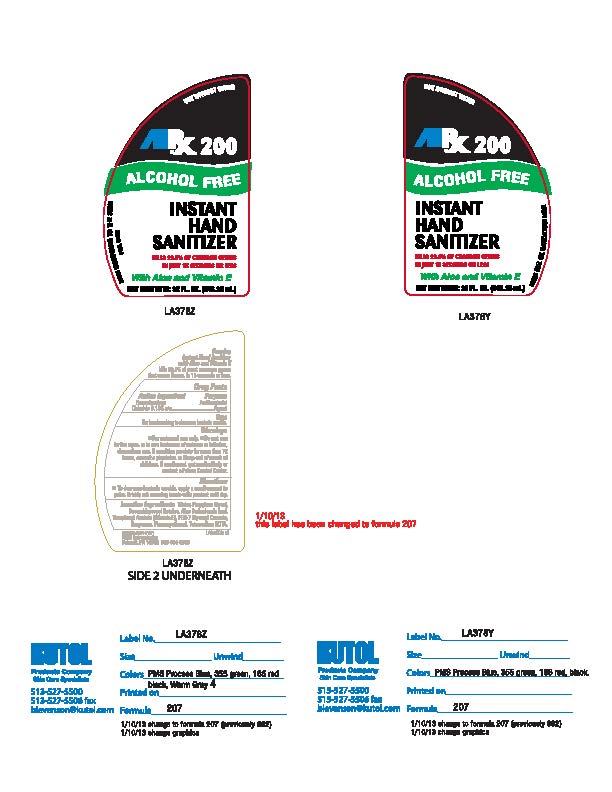 DRUG LABEL: RX200 Foaming Instant Hand Sanitizer
NDC: 57356-207 | Form: LIQUID
Manufacturer: The Bullen Companies, Inc.
Category: otc | Type: HUMAN OTC DRUG LABEL
Date: 20130426

ACTIVE INGREDIENTS: BENZALKONIUM CHLORIDE 4.918 g/100 mL
INACTIVE INGREDIENTS: COCAMIDOPROPYL BETAINE 18.915 g/100 mL; WATER 98.258 mL/100 mL; PEG-7 GLYCERYL COCOATE 4.918 g/100 mL; PROPYLENE GLYCOL 18.915 g/100 mL; PHENOXYETHANOL 15.132 g/100 mL; MONOSODIUM ETHYLENEDIAMINETETRAACETATE 1.51318 g/100 mL; ALOE VERA LEAF 0.000083 g/100 mL; .ALPHA.-TOCOPHEROL ACETATE, DL- 0.000083 g/100 mL

RX200 Foaming Instant Hand Sanitizer

Uses

Products 17 & 78: For handwashing to decrease bacteria on skin.

Product 41: Hand sanitizer to help reduce bacteria on the skin that could cause disease. Recommended for repeated use.

Purpose

Products 17 & 78: Antibacterial Agent

Product 41: Antibacterial Handwashing

Active Ingredient

Benzalkonium Chloride 0.13% w/w

Warnings

Products 17 & 41: For external use only. Avoid contact with eyes. If contact occurs, flush with water. Stop use and ask a doctor if, in rare instances, redness or irritations develops. If condition persists for more than 72 hours, consult a physician. Keep out of reach of children. If swallowed, get medical help or contact a Poison Control Center.

Product 78: For external use only. Do not use in the eyes. In rare instances of redness or irritation, discontinue use. If condition persists for more than 72 hours, consult a physician. Keep out of reach of children. If swallowed, get medical help or contact a Poison Control Center.

Inactive Ingredients

Water, Propylene Glycol, Cocamidopropyl Betaine, Aloe Barbadensis Leaf, Tocopheryl Acetate (Vitamin E), PEG-7 Glyceryl Cocoate, Fragrance, Phenoxyethanol, Tetrasodium EDTA.

Directions

To decrease bacteria on skin, apply a small amount to palm. Briskly rub covering hands with product until dry.

Warnings

Keep out of reach of children. If swallowed, get medical help or contact a Poison Control Center.